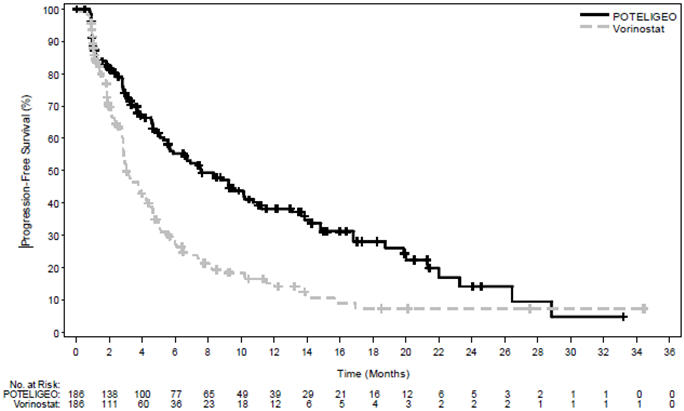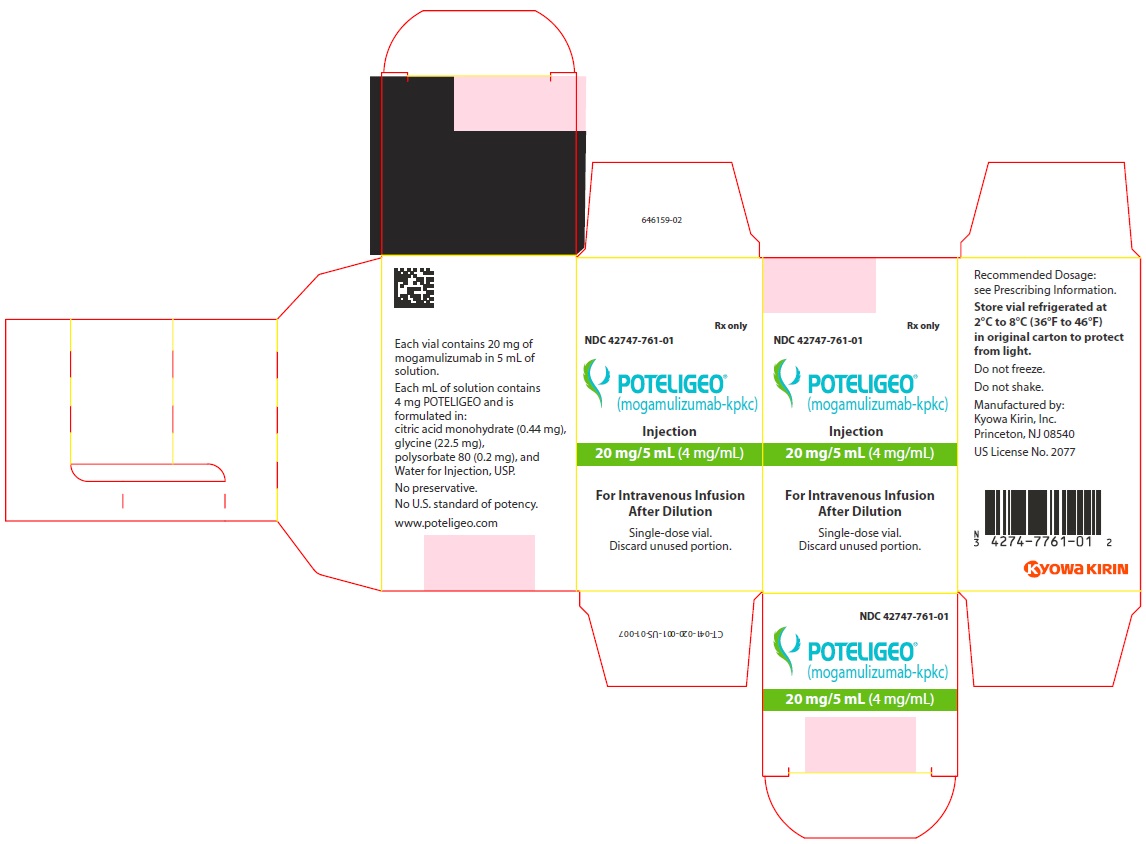 DRUG LABEL: POTELIGEO
NDC: 42747-761 | Form: INJECTION
Manufacturer: Kyowa Kirin, Inc.
Category: prescription | Type: HUMAN PRESCRIPTION DRUG LABEL
Date: 20260302

ACTIVE INGREDIENTS: mogamulizumab 4 mg/1 mL
INACTIVE INGREDIENTS: citric acid monohydrate 2.2 mg/1 mL; glycine 112.5 mg/1 mL; polysorbate 80 1 mg/1 mL; sodium hydroxide; hydrochloric acid; water

HIGHLIGHTS OF PRESCRIBING INFORMATION

These highlights do not include all the information needed to use POTELIGEO safely and effectively. See full prescribing information for POTELIGEO.
POTELIGEO® (mogamulizumab-kpkc) injection, for intravenous use
Initial U.S. Approval: 2018

1 INDICATIONS AND USAGE

POTELIGEO is a CC chemokine receptor type 4 (CCR4)-directed monoclonal antibody indicated for the treatment of adult patients with relapsed or refractory mycosis fungoides or Sézary syndrome after at least one prior systemic therapy (1).

2 DOSAGE AND ADMINISTRATION

1 mg/kg as an intravenous infusion over at least 60 minutes on days 1, 8, 15, and 22 of the first 28-day cycle and on days 1 and 15 of each subsequent cycle (2).

3 DOSAGE FORMS AND STRENGTHS

Injection: 20 mg/5 mL (4 mg/mL) solution in a single-dose vial (3).

4 CONTRAINDICATIONS

None (4).

5 WARNINGS AND PRECAUTIONS

- Dermatologic Toxicity: Temporarily interrupt POTELIGEO for moderate or severe skin rashes. Permanently discontinue POTELIGEO for life-threatening rash (5.1).
- Infusion Reactions: Temporarily interrupt POTELIGEO for any infusion reaction. Permanently discontinue POTELIGEO for any life-threatening infusion reaction (5.2).
- Infections: Monitor and treat promptly (5.3).
- Autoimmune Complications: Interrupt or permanently discontinue POTELIGEO as appropriate (5.4).
- Complications of Allogeneic HSCT after POTELIGEO: Monitor for severe acute graft-versus-host disease (GVHD) and steroid-refractory GVHD. Transplant-related mortality has occurred (5.5).

6 ADVERSE REACTIONS

The most common adverse reactions (reported in ≥20% of patients) are rash, infusion related reactions, fatigue, diarrhea, musculoskeletal pain, and upper respiratory tract infection (6.1).

To report SUSPECTED ADVERSE REACTIONS, contact Kyowa Kirin, Inc. at 1-844-768-3544 or FDA at 1-800-FDA-1088 or www.fda.gov/medwatch.

FULL PRESCRIBING INFORMATION

1 INDICATIONS AND USAGE

POTELIGEO is indicated for the treatment of adult patients with relapsed or refractory mycosis fungoides (MF) or Sézary syndrome (SS) after at least one prior systemic therapy.

2 DOSAGE AND ADMINISTRATION

2.1 Recommended Dosage

The recommended dose of POTELIGEO is 1 mg/kg administered as an intravenous infusion over at least 60 minutes. Administer on days 1, 8, 15, and 22 of the first 28-day cycle, then on days 1 and 15 of each subsequent 28-day cycle until disease progression or unacceptable toxicity.

Administer POTELIGEO within 2 days of the scheduled dose. If a dose is missed, administer the next dose as soon as possible and resume dosing schedule.

Do not administer POTELIGEO subcutaneously or by rapid intravenous administration.

Recommended Premedications

Administer premedication with diphenhydramine and acetaminophen for the first POTELIGEO infusion.

2.2 Dose Modifications for Toxicity

Dermatologic Toxicity

- Permanently discontinue POTELIGEO for life-threatening (Grade 4) rash or for any Stevens-Johnson syndrome (SJS) or toxic epidermal necrolysis (TEN) [see Warnings and Precautions (5.1)]. If SJS or TEN is suspected, stop POTELIGEO and do not resume unless SJS or TEN has been excluded and the cutaneous reaction has resolved to Grade 1 or less.
- If moderate or severe (Grades 2 or 3) rash occurs, interrupt POTELIGEO and administer at least 2 weeks of topical corticosteroids. If rash improves to Grade 1 or less, POTELIGEO may be resumed [see Warnings and Precautions (5.1)].
- If mild (Grade 1) rash occurs, consider topical corticosteroids.

Infusion Reactions

- Permanently discontinue POTELIGEO for a life-threatening (Grade 4) infusion reaction [see Warnings and Precautions (5.2)].
- Temporarily interrupt the infusion of POTELIGEO for mild to severe (Grades 1 to 3) infusion reactions and treat symptoms. Reduce the infusion rate by at least 50% when restarting the infusion after symptoms resolve. If reaction recurs and is unmanageable, discontinue infusion. [see Warnings and Precautions (5.2)].
- If an infusion reaction occurs, administer premedication (such as diphenhydramine and acetaminophen) for subsequent POTELIGEO infusions.

2.3 Preparation and Administration

Preparation

- Visually inspect drug product solution for particulate matter and discoloration prior to administration. POTELIGEO is a clear to slightly opalescent colorless solution. Discard the vial if cloudiness, discoloration, or particulates are observed.
- Calculate the dose (mg/kg) and number of vials of POTELIGEO needed to prepare the infusion solution based on patient weight.
- Aseptically withdraw the required volume of POTELIGEO into the syringe and transfer into an intravenous (IV) bag containing 0.9% Sodium Chloride Injection, USP. The final concentration of the diluted solution should be between 0.1 mg/mL to 3 mg/mL.
- Mix diluted solution by gentle inversion. Do not shake.
- Discard any unused portion left in the vial.

The diluted solution is compatible with polyvinyl chloride (PVC) or polyolefin (PO) infusion bags.

Administration

- Administer infusion solution over at least 60 minutes through an intravenous line containing a sterile, low protein binding, 0.22 micron (or equivalent) in-line filter.
- Do not mix POTELIGEO with other drugs.
- Do not co-administer other drugs through the same intravenous line.

Storage of Diluted Solution

After preparation, infuse the POTELIGEO solution immediately, or store under refrigeration at 2°C to 8°C (36°F to 46°F) for no more than 24 hours from the time of infusion preparation.

Do not freeze. Do not shake.

3 DOSAGE FORMS AND STRENGTHS

Injection: 20 mg/5 mL (4 mg/mL) as a clear to slightly opalescent colorless solution in a single-dose vial.

4 CONTRAINDICATIONS

None.

5 WARNINGS AND PRECAUTIONS

5.1 Dermatologic Toxicity

Fatal and life-threatening skin adverse reactions, including Stevens-Johnson syndrome (SJS) and toxic epidermal necrolysis (TEN), have occurred in recipients of POTELIGEO. Rash (drug eruption) is one of the most common adverse reactions associated with POTELIGEO. In Study 0761-010, 25% (80/319) of patients treated with POTELIGEO had an adverse reaction of drug eruption, with 18% of these cases being severe (Grade 3) and 82% of these cases being Grade 1 or 2. Of 528 patients treated with POTELIGEO in clinical trials, Grade 3 skin adverse reactions were reported in 3.6%, Grade 4 skin adverse reactions in <1%, and SJS in <1%.

The onset of drug eruption is variable, and the affected areas and appearance vary. In Study 0761-010, the median time to onset was 15 weeks, with 25% of cases occurring after 31 weeks. The more common presentations reported included papular or maculopapular rash, lichenoid, spongiotic or granulomatous dermatitis, and morbilliform rash. Other presentations included scaly plaques, pustular eruption, folliculitis, non-specific dermatitis, and psoriasiform dermatitis.

Monitor patients for rash throughout the treatment course. Management of dermatologic toxicity includes topical corticosteroids and interruption or permanent cessation of POTELIGEO [see Dosage and Administration (2.2)]. Consider skin biopsy to help distinguish drug eruption from disease progression.

Discontinue POTELIGEO permanently for SJS or TEN or for any life-threatening (Grade 4) reaction. For possible SJS or TEN, interrupt POTELIGEO and do not restart unless SJS or TEN is ruled out and the cutaneous reaction has resolved to Grade 1 or less.

5.2 Infusion Reactions

Fatal and life-threatening infusion reactions have been reported in patients treated with POTELIGEO. In Study 0761-010, infusion reactions occurred in 35% (112/319) of patients treated with POTELIGEO, with 8% of these reactions being severe (Grade 3). Most reactions (approximately 90%) occur during or shortly after the first infusion. Infusion reactions can also occur with subsequent infusions. The most commonly reported signs include chills, nausea, fever, tachycardia, rigors, headache, and vomiting.

Consider premedication (such as diphenhydramine and acetaminophen) for the first infusion of POTELIGEO in all patients. Whether premedication reduces the risk or severity of these reactions is not established. In Study 0761-010, infusion reactions occurred in 42% of patients without premedication and 32% of patients with premedication. Monitor patients closely for signs and symptoms of infusion reactions and interrupt the infusion for any grade reaction and treat promptly [see Dosage and Administration (2.2)].

5.3 Infections

Fatal and life-threatening infections have occurred in patients treated with POTELIGEO, including sepsis, pneumonia, and skin infection. In Study 0761-010, 18% (34/184) of patients randomized to POTELIGEO had Grade 3 or higher infection or an infection-related serious adverse reaction. Monitor patients for signs and symptoms of infection and treat promptly.

5.4 Autoimmune Complications

Fatal and life-threatening immune-mediated complications have been reported in recipients of POTELIGEO. Grade 3 or higher immune-mediated or possibly immune-mediated reactions have included myositis, myocarditis, polymyositis, hepatitis, pneumonitis, glomerulonephritis and a variant of Guillain-Barré syndrome. Use of systemic immunosuppressants for immune-mediated reactions was reported in 1.9% (6/319) of recipients of POTELIGEO in Study 0761-010, including for a case of Grade 2 polymyalgia rheumatica. New-onset hypothyroidism (Grade 1 or 2) was reported in 1.3% of patients and managed with observation or levothyroxine. Interrupt or permanently discontinue POTELIGEO as appropriate for suspected immune-mediated adverse reactions. Consider the benefit/risk of POTELIGEO in patients with a history of autoimmune disease.

5.5 Complications of Allogeneic Hematopoietic Stem Cell Transplantation (HSCT) after POTELIGEO

Increased risks of transplant complications have been reported in patients who receive allogeneic HSCT after POTELIGEO including severe (Grade 3 or 4) acute graft-versus-host disease (GVHD), steroid-refractory GVHD, and transplant-related death. Among recipients of pre-transplantation POTELIGEO, a higher risk of transplant complications has been reported if POTELIGEO is given within a shorter time frame (approximately 50 days) before HSCT. Follow patients closely for early evidence of transplant-related complications.

6 ADVERSE REACTIONS

The following serious adverse reactions are discussed in greater detail in other sections of the labeling:

- Dermatologic Toxicity [see Warnings and Precautions (5.1)].
- Infusion Reactions [see Warnings and Precautions (5.2)].
- Infections [see Warnings and Precautions (5.3)].
- Autoimmune Complications [see Warnings and Precautions (5.4)].
- Complications of Allogeneic HSCT after POTELIGEO [see Warnings and Precautions (5.5)].

6.1 Clinical Trial Experience

Because clinical trials are conducted under widely varying conditions, adverse reaction rates observed in the clinical trials of a drug cannot be directly compared to rates in the clinical trials of another drug and may not reflect the rates observed in practice.

The data described below reflect exposure to POTELIGEO in Study 0761-010, a randomized, open-label, actively controlled clinical trial for adult patients with MF or SS who received at least one prior systemic therapy [see Clinical Studies (14)]. Of 370 patients treated, 184 (57% with MF, 43% with SS) received POTELIGEO as randomized treatment and 186 (53% with MF, 47% with SS) received vorinostat. In the vorinostat arm, 135 patients (73%) subsequently crossed over to POTELIGEO for a total of 319 patients treated with POTELIGEO.

POTELIGEO was administered at 1 mg/kg intravenously over at least 60 minutes on days 1, 8, 15, and 22 of the first 28-day cycle and on days 1 and 15 of subsequent 28-day cycles. Premedication (diphenhydramine, acetaminophen) was optional and administered to 65% of randomized patients for the first infusion. The comparator group received vorinostat 400 mg orally once daily, given continuously in 28-day cycles. Treatment continued until unacceptable toxicity or progressive disease.

The median age was 64 years (range, 25 to 101 years), 58% of patients were male, 70% were white, and 99% had an Eastern Cooperative Oncology Group (ECOG) performance status of 0 or 1. Patients had a median of 3 prior systemic therapies. The trial required an absolute neutrophil count (ANC) ≥1,500/µL (≥1,000/µL if bone marrow was involved), platelet count ≥100,000/µL (≥75,000/µL if bone marrow was involved), creatinine clearance >50 mL/min or serum creatinine ≤1.5 mg/dL, and hepatic transaminases ≤2.5 times upper limit of normal (ULN) (≤5 times ULN if lymphomatous liver infiltration). Patients with active autoimmune disease, active infection, autologous HSCT within 90 days, or prior allogeneic HSCT were excluded.

During randomized treatment, the median duration of exposure to POTELIGEO was 5.6 months, with 48% (89/184) of patients with at least 6 months of exposure and 23% (43/184) with at least 12 months of exposure. The median duration of exposure to vorinostat was 2.8 months, with 22% (41/186) of patients with at least 6 months of exposure.

Fatal adverse reactions within 90 days of the last dose occurred in 2.2% (7/319) of patients who received POTELIGEO as randomized or crossover treatment.

Serious adverse reactions were reported in 36% (66/184) of patients randomized to POTELIGEO and most often involved infection (16% of patients; 30/184). Serious adverse reactions reported in >2% of patients randomized to POTELIGEO were pneumonia (5%), sepsis (4%), pyrexia (4%), and skin infection (3%); other serious adverse reactions, each reported in 2% of patients, included hepatitis, pneumonitis, rash, infusion related reaction, lower respiratory tract infection, and renal insufficiency. POTELIGEO was discontinued for adverse reactions in 18% of randomized patients, most often due to rash or drug eruption (7.1%).

The most common adverse reactions (reported in ≥20% of patients randomized to POTELIGEO) were rash (including drug eruption), infusion related reactions, fatigue, diarrhea, upper respiratory tract infection and musculoskeletal pain. Other common adverse reactions (reported in ≥10% of patients randomized to POTELIGEO) included skin infection, pyrexia, nausea, edema, thrombocytopenia, headache, constipation, mucositis, anemia, cough and hypertension. Table 1 summarizes common adverse reactions having a ≥2% higher incidence with POTELIGEO than with vorinostat in Study 0761-010.

Table 1: Common Adverse Reactions (≥10%) with ≥2% Higher Incidence in the POTELIGEO Arm
Adverse Reactions by Body System [Adverse reactions include groupings of individual preferred terms.] , [Includes adverse reactions reported up to 90 days after randomized treatment.] | POTELIGEO (N=184) |  | Vorinostat (N=186)
Adverse Reactions by Body System [Adverse reactions include groupings of individual preferred terms.] , [Includes adverse reactions reported up to 90 days after randomized treatment.] | All Grades (%) | ≥Grade 3 (%) | All Grades (%) | ≥Grade 3 (%)
Skin and Subcutaneous Tissue Disorders
Rash, Including Drug Eruption | 35 | 5 | 11 | 2
Drug Eruption | 24 | 5 | <1 | 0
Procedural Complications
Infusion Related Reaction | 33 | 2 | 0 | 0
Infections
Upper Respiratory Tract Infection | 22 | 0 | 16 | 1
Skin Infection | 19 | 3 | 13 | 4
Musculoskeletal and Connective Tissue Disorders
Musculoskeletal Pain | 22 | <1 | 17 | 3
General Disorders
Pyrexia | 17 | <1 | 7 | 0
Gastrointestinal
Mucositis | 12 | 1 | 6 | 0
Rash/Drug Eruption includes: dermatitis (allergic, atopic, bullous, contact, exfoliative, infected), drug eruption, palmoplantar keratoderma, rash (generalized, macular, maculopapular, papular, pruritic, pustular), skin reaction, toxic skin eruption
Upper Respiratory Tract Infection includes: laryngitis viral, nasopharyngitis, pharyngitis, rhinitis, sinusitis, upper respiratory tract infection, viral upper respiratory tract infection
Skin Infection includes: cellulitis, dermatitis infected, erysipelas, impetigo, infected skin ulcer, periorbital cellulitis, skin bacterial infection, skin infection, staphylococcal skin infection
Musculoskeletal Pain includes: back pain, bone pain, musculoskeletal chest pain, musculoskeletal pain, myalgia, neck pain, pain in extremity
Mucositis includes: aphthous stomatitis, mouth ulceration, mucosal inflammation, oral discomfort, oral pain, oropharyngeal pain, stomatitis

Other Common Adverse Reactions in ≥10% of POTELIGEO Arm [Includes grouped terms] , [From 184 patients randomized to POTELIGEO]

- General disorders: fatigue (31%), edema (16%)
- Gastrointestinal disorders: diarrhea (28%), nausea (16%), constipation (13%)
- Blood and lymphatic system disorders: thrombocytopenia (14%), anemia (12%)
- Nervous system disorders: headache (14%)
- Vascular disorders: hypertension (10%)
- Respiratory disorders: cough (11%)

Adverse Reactions in ≥5% but <10% of POTELIGEO Arm ,

- Infections: candidiasis (9%), urinary tract infection (9%), folliculitis (8%), pneumonia (6%), otitis (5%), herpesvirus infection (5%)
- Investigations: renal insufficiency (9%), hyperglycemia (9%), hyperuricemia (8%), weight increase (8%), weight decrease (6%), hypomagnesemia (6%)
- Psychiatric disorders: insomnia (9%), depression (7%)
- Skin and subcutaneous disorders: xerosis (8%), alopecia (7%)
- Nervous system disorders: dizziness (8%), peripheral neuropathy (7%)
- Metabolism and nutrition disorders: decreased appetite (8%)
- Respiratory disorders: dyspnea (7%)
- General disorders: chills (7%)
- Gastrointestinal disorders: vomiting (7%), abdominal pain (5%)
- Injury, poisoning and procedural complications: fall (6%)
- Musculoskeletal disorders: muscle spasms (5%)
- Cardiovascular disorders: arrhythmia (5%)
- Eye disorders: conjunctivitis (5%)

Selected Other Adverse Reactions ,

- Tumor lysis syndrome (<1%)
- Myocardial ischemia or infarction (<1%)
- Cardiac failure (<1%)
- Cytomegalovirus infection (<1%)

Table 2 summarizes common treatment-emergent laboratory abnormalities having a ≥2% higher incidence with POTELIGEO than with vorinostat.

Table 2: Common New or Worsening Laboratory Abnormalities (≥10%) with ≥2% Higher Incidence in the POTELIGEO Arm
Laboratory Test [Includes laboratory abnormalities, reported up to 90 days after treatment, that are new or worsening in grade or with worsening from baseline unknown.] | POTELIGEO (N=184) |  | Vorinostat (N=186)
Laboratory Test [Includes laboratory abnormalities, reported up to 90 days after treatment, that are new or worsening in grade or with worsening from baseline unknown.] | All Grades (%) | ≥Grade 3 (%) | All Grades (%) | ≥Grade 3 (%)
Chemistry
Albumin Decreased | 34 | 2 | 27 | 3
Calcium Decreased | 30 | 3 | 20 | 2
Uric Acid Increased | 29 | 29 | 11 | 11
Phosphate Decreased | 27 | 5 | 26 | 5
Magnesium Decreased | 17 | <1 | 8 | <1
Glucose Decreased | 14 | 0 | 8 | <1
Calcium Increased | 12 | <1 | 8 | <1
Hematology
CD4 Lymphocytes Decreased [Out of 99 evaluable recipients of POTELIGEO and 36 evaluable recipients of vorinostat.] | 63 | 43 | 17 | 8
Lymphocytes Decreased | 31 | 16 | 12 | 4
White Blood Cells Decreased | 33 | 2 | 18 | 2

Other common treatment-emergent laboratory abnormalities in the POTELIGEO arm included hyperglycemia (52%; 4% Grade 3-4), anemia (35%; 2% Grade 3-4), thrombocytopenia (29%, none Grade 3-4), aspartate transaminase (AST) increased (25%; 2% Grade 3-4), alanine transaminase (ALT) increased (18%; 1% Grade 3-4), alkaline phosphatase increased (17%; 0% Grade 3-4), and neutropenia (10%; 2% Grade 3-4). Grade 4 treatment-emergent laboratory abnormalities observed in ≥1% of the POTELIGEO arm included lymphopenia (5%), leukopenia (1%), and hypophosphatemia (1%).

6.2 Postmarketing Experience

The following adverse reactions have been identified during post-approval use of POTELIGEO. Because these reactions are reported voluntarily from a population of uncertain size, it is not always possible to reliably estimate their frequency or establish a causal relationship to drug exposure.

- Gastrointestinal disorders: Immune-mediated colitis
- Infections: Hepatitis B virus reactivation
- Cardiac disorders: Stress cardiomyopathy
- Skin and subcutaneous disorders: Granuloma

8 USE IN SPECIFIC POPULATIONS

8.1 Pregnancy

Risk Summary

There are no available data on POTELIGEO use in pregnant women to inform a drug-associated risk of major birth defects and miscarriage. In an animal reproduction study, administration of mogamulizumab-kpkc to pregnant cynomolgus monkeys from the start of organogenesis through delivery did not show a potential for adverse developmental outcomes at maternal systemic exposures 27 times the exposure in patients at the recommended dose, based on AUC (see Data). In general, IgG molecules are known to cross the placental barrier and in the monkey reproduction study mogamulizumab-kpkc was detected in fetal plasma. Therefore, POTELIGEO has the potential to be transmitted from the mother to the developing fetus. POTELIGEO is not recommended during pregnancy or in women of childbearing potential not using contraception.

The estimated background risk of major birth defects and miscarriage for the indicated population is unknown. All pregnancies have a background risk of birth defect, loss, or other adverse outcomes. In the U.S. general population, the estimated background risks of major birth defects and miscarriage in clinically recognized pregnancies are 2-4% and 15-20%, respectively.

Data

Animal Data

The effects of mogamulizumab-kpkc on embryo-fetal development were evaluated in 12 pregnant cynomolgus monkeys that received mogamulizumab-kpkc once weekly by intravenous administration from the start of organogenesis through delivery at an exposure level 27 times higher than the clinical dose. Mogamulizumab-kpkc administration did not show a potential for embryo-fetal lethality, teratogenicity, or fetal growth retardation and did not result in spontaneous abortion or increased fetal death. In surviving fetuses (10 of 12 compared with 11 of 12 in the control group) of cynomolgus monkeys treated with mogamulizumab-kpkc, a decrease in CCR4-expressing lymphocytes due to the pharmacological activity of mogamulizumab-kpkc was noted; there were no apparent mogamulizumab-kpkc -related external, visceral, or skeletal abnormalities.

8.2 Lactation

Risk Summary

There is no information regarding the presence of POTELIGEO in human milk, the effects on the breastfed child, or the effects on milk production. The developmental and health benefits of breastfeeding should be considered along with the mother's clinical need for POTELIGEO and any potential adverse effects on the breastfed child from POTELIGEO or from the underlying maternal condition.

8.3 Females and Males of Reproductive Potential

POTELIGEO is not recommended during pregnancy or in women of childbearing potential not using contraception.

Pregnancy Testing

For females of reproductive potential, verify pregnancy status prior to initiating POTELIGEO.

Contraception

Advise females of reproductive potential to use effective contraception during treatment with POTELIGEO and for 3 months following the last dose of POTELIGEO.

8.4 Pediatric use

The safety and effectiveness of POTELIGEO in pediatric patients have not been established.

8.5 Geriatric use

Of 319 patients with MF or SS who received POTELIGEO in Study 0761-010, 162 (51%) were ≥65 years. No overall differences in effectiveness were observed between these patients and younger patients. In patients aged ≥65, Grade 3 or higher adverse reactions were reported in 45% and serious adverse reactions in 36%, whereas in patients aged <65, Grade 3 or higher adverse reactions were reported in 36% and serious adverse reactions in 29%.

11 DESCRIPTION

Mogamulizumab-kpkc is a recombinant humanized monoclonal antibody that targets CC chemokine receptor 4 (CCR4)-expressing cells. Mogamulizumab-kpkc is an IgG1 kappa immunoglobulin that has a calculated molecular mass of approximately 149 kDa. Mogamulizumab-kpkc is produced by recombinant DNA technology in Chinese hamster ovary cells.

POTELIGEO (mogamulizumab-kpkc) injection is a sterile, ready-to-use, preservative-free, clear to slightly opalescent colorless solution in a single-dose vial for dilution prior to intravenous infusion. Each vial contains 20 mg of mogamulizumab-kpkc in 5 mL of solution. Each mL of solution contains 4 mg of mogamulizumab-kpkc and is formulated in: citric acid monohydrate (0.44 mg), glycine (22.5 mg), polysorbate 80 (0.2 mg), and Water for Injection, USP. May contain hydrochloric acid/sodium hydroxide to adjust pH to 5.5.

12 CLINICAL PHARMACOLOGY

12.1 Mechanism of Action

Mogamulizumab-kpkc is a defucosylated, humanized IgG1 kappa monoclonal antibody that binds to CCR4, a G protein-coupled receptor for CC chemokines that is involved in the trafficking of lymphocytes to various organs. Non-clinical in vitro studies demonstrate mogamulizumab-kpkc binding targets a cell for antibody-dependent cellular cytotoxicity (ADCC) resulting in depletion of the target cells. CCR4 is expressed on the surface of some T-cell malignancies and is expressed on regulatory T-cells (Treg) and a subset of Th2 T-cells.

12.2 Pharmacodynamics

Mogamulizumab-kpkc exposure-response relationships and the time course of pharmacodynamics response are unknown.

12.3 Pharmacokinetics

Mogamulizumab-kpkc pharmacokinetics (PK) was evaluated in patients with T-cell malignancies. Parameters are presented as the geometric mean [% coefficient of variation (%CV)] unless otherwise specified. Mogamulizumab-kpkc concentrations increased proportionally with dose over the dose range of 0.01 to 1.0 mg/kg (0.01 to 1 times the approved recommended dosage).

Following repeated dosing of the approved recommended dosage, steady state concentrations were reached after 8 doses (12 weeks), and the systemic accumulation was 1.6-fold. At steady state, the peak concentration (Cmax,ss) is 32 (68%) µg/mL, the trough concentration (Cmin,ss) is 11 (239%) µg/mL, and AUCss is 5,577 (125%) µg∙hr/mL.

Distribution

The central volume of distribution is 3.6 L (20%).

Elimination

The terminal half-life is 17 days (66%), and the clearance is 12 mL/h (84%).

Specific Populations:

No clinically significant changes in the PK of mogamulizumab-kpkc were observed based on age (range: 22 to 101 years), sex, ethnicity, renal impairment (creatinine clearance <90 mL/min, estimated by Cockcroft-Gault), mild (total bilirubin ≤ ULN and AST <ULN, or total bilirubin <1 to 1.5 times ULN and any AST) or moderate (total bilirubin >1.5 to 3 times ULN and any AST) hepatic impairment, disease subtype (MF or SS), degree of CCR4 expression, or ECOG status. The effect of severe hepatic impairment (total bilirubin >3 times ULN and any AST) on mogamulizumab-kpkc PK is unknown.

Drug Interaction Studies

No drug interaction studies have been conducted with POTELIGEO.

12.6 Immunogenicity

As with all therapeutic proteins, there is a potential for immunogenicity. The detection of antibody formation is highly dependent on the sensitivity and specificity of the assay. Additionally, the observed incidence of antibody (including neutralizing antibody) positivity in an assay may be influenced by several factors, including assay methodology, sample handling, timing of sample collection, concomitant medications, and underlying disease. For these reasons, comparison of incidence of antibodies to POTELIGEO with the incidences of antibodies in other studies or to other products may be misleading.

Among 313 patients treated with POTELIGEO and whose antibodies were tested, 44 (14.1%) tested positive for anti-mogamulizumab-kpkc antibodies. There was no identified clinically significant effect of anti-drug antibodies on pharmacokinetics, safety, or effectiveness of POTELIGEO. There were no positive neutralizing antibody responses.

13 NONCLINICAL TOXICOLOGY

13.1 Carcinogenesis, Mutagenesis, and Impairment of Fertility

No carcinogenicity or genotoxicity studies have been conducted with POTELIGEO.

No specific studies have been conducted to evaluate potential effects of POTELIGEO on fertility. No mogamulizumab-kpkc -related toxic effects in the male and female reproductive organs were observed in sexually mature monkeys in repeat-dose toxicology studies up to 26 weeks in duration.

14 CLINICAL STUDIES

A randomized, open-label, multicenter trial (Study 0761-010; NCT01728805) evaluated the efficacy of POTELIGEO in adult patients with MF or SS after at least one prior systemic therapy. The trial randomized 372 patients 1:1 to either POTELIGEO (186 patients; 56% with MF, 44% with SS) or vorinostat (186 patients; 53% with MF, 47% with SS). The trial included patients regardless of tumor CCR4 expression status and excluded patients with histologic transformation, prior allogeneic HSCT, autologous HSCT within 90 days, active autoimmune disease, or active infection. The trial required patients to have ANC ≥1,500/µL (≥1,000/µL if bone marrow was involved), platelet count ≥100,000/µL (≥75,000/µL if bone marrow was involved), creatinine clearance >50 mL/min or serum creatinine ≤1.5 mg/dL and hepatic transaminases ≤2.5 times ULN (≤5 times ULN if lymphomatous liver infiltration).

The dose of POTELIGEO was 1 mg/kg administered intravenously over at least 60 minutes on days 1, 8, 15, and 22 of the first 28-day cycle and on days 1 and 15 of each subsequent cycle. Vorinostat was dosed at 400 mg orally once daily, continuously for 28-day cycles. Treatment continued until disease progression or unacceptable toxicity. Vorinostat-treated patients with disease progression or unacceptable toxicities were permitted to cross over to POTELIGEO.

The median age was 64 years (range: 25 to 101), 58% of patients were male, and 70% were white. At study baseline, 38% had stage IB-II disease, 10% stage III, and 52% stage IV. The median number of prior systemic therapies was 3. In the POTELIGEO arm, baseline CCR4 expression status by immunohistochemistry was available in 140 patients (75%), of whom all had CCR4 detected on ≥1% of lymphocytes on skin biopsy, and 134/140 (96%) had CCR4 detected on ≥10% of the lymphocytes. CCR4 expression status was similar in the vorinostat arm.

During randomized treatment, the median duration of exposure to POTELIGEO was 5.6 months (range: <1 to 45.3 months), with 48% of patients with at least 6 months of exposure and 23% with at least 12 months of exposure. The median duration of exposure to vorinostat was 2.8 months (range: <1 to 34.8 months), with 22% of patients with at least 6 months of exposure.

Efficacy was based on investigator-assessed progression-free survival (PFS), which was defined as the time from the date of randomization until documented progression of disease or death. Other efficacy measures included overall response rate (ORR) based on global composite response criteria that combine measures from each disease compartment (skin, blood, lymph nodes and viscera). Responses required confirmation at two successive disease assessments, which included the modified Severity Weighted Assessment Tool, skin photographs, central flow cytometry, and computed tomography.

The trial demonstrated that POTELIGEO significantly prolonged PFS compared to vorinostat (Table 3). The Kaplan-Meier curve for PFS by investigator is shown in Figure 1. The estimated median follow-up for investigator-assessed PFS was 13 months in the POTELIGEO arm and 10.4 months in the vorinostat arm. By independent review committee assessment, the estimated median PFS was 6.7 months (95% CI, 5.6 to 9.4) in the POTELIGEO arm and 3.8 months (95% CI, 3.0 to 4.7) in the vorinostat arm (hazard ratio 0.64; 95% CI: 0.49, 0.84).

Figure 1 Kaplan-Meier Curve for Progression-Free Survival per Investigator

Table 3 also summarizes investigator-assessed confirmed response rates, overall and by disease compartment. The trial demonstrated improvement in ORR with POTELIGEO.

Table 3 Efficacy of Randomized Treatment
Outcome per Investigator | POTELIGEO N=186 | Vorinostat N=186
PFS
Number of events, n | 110 | 131
Progressive disease | 104 | 128
Death | 6 | 3
Median PFS (95% CI) (months) [Kaplan-Meier estimate.] | 7.6 (5.6, 10.2) | 3.1 (2.8, 4.0)
Hazard ratio (95% CI) Log rank p-value | 0.53 (0.41, 0.69) <.001
Overall response rate (confirmed CR + PR), n (%) [Based on Global Composite Response score.] , [Responses in blood and skin must have persisted for at least 4 weeks to be considered confirmed and were evaluated every 4 weeks for the first year. Responses in lymph nodes, visceral disease and overall were evaluated every 8 weeks for the first year.] | 52 (28) | 9 (5)
95% CI | (22, 35) | (2, 9)
P-value [From Cochran-Mantel-Haenszel test adjusted for disease type, stage, and region.] | <.001
Duration of overall response (months)
Median (95% CI) | 13.9 (9.3, 18.9) | 9.0 (4.6, NE)
Confirmed best overall response
CR, n (%) | 4 (2) | 0 (0)
95% CI | (1, 5) | (0, 2)
PR, n (%) | 47 (25) | 9 (5)
95% CI | (20, 33) | (2, 9)
Response by compartment (confirmed CR + PR)
Blood | n=124 | n=125
Response rate, n (%) | 83 (67) | 23 (18)
95% CI | (58, 75) | (12, 26)
Skin | n=186 | n=186
Response rate, n (%) | 78 (42) | 29 (16)
95% CI | (35, 49) | (11, 22)
Lymph nodes | n=136 | n=133
Response rate, n (%) | 21 (15) | 5 (4)
95% CI | (10, 23) | (1, 9)
Viscera | n=6 | n=4
Response rate, n (%) | 0 (0) | 0 (0)
95% CI | (0, 46) | (0, 60)
CI=confidence interval; CR=complete response; NE=not estimable; PR=partial response

16 HOW SUPPLIED/STORAGE AND HANDLING

POTELIGEO (mogamulizumab-kpkc) injection is a sterile, preservative-free, clear to slightly opalescent colorless solution supplied in a carton containing one 20 mg/5 mL (4 mg/mL), single-dose glass vial (NDC 42747-761-01).

STORAGE AND HANDLING

Store vials under refrigeration at 2°C to 8°C (36°F to 46°F) in original package to protect from light until time of use. Do not freeze. Do not shake.

17 PATIENT COUNSELING INFORMATION

Advise the patient to read the FDA-approved patient labeling (Patient Information).

Inform patients of the risk of the following adverse reactions that may require additional treatment and/or withholding or discontinuation of POTELIGEO including:

- Dermatological Toxicity: Advise patients to contact their healthcare provider immediately for new or worsening skin rash [see Warnings and Precautions (5.1)]. Advise patients that the rash can happen at any time while receiving POTELIGEO.
- Infusion Reactions: Advise patients to contact their healthcare provider immediately for signs or symptoms of infusion reactions [see Warnings and Precautions (5.2)].
- Infections: Advise patients to contact their health care provider immediately for fever or other evidence of infection [see Warnings and Precautions (5.3)].
- Autoimmune Complications: Advise patients to notify their healthcare provider of any history of autoimmune disease [see Warnings and Precautions (5.4)].
- Complications of Allogeneic HSCT after POTELIGEO: Advise patients of potential risk of post-transplant complications [see Warnings and Precautions (5.5)].
- Females of Reproductive Potential: Advise use of effective contraception during treatment with POTELIGEO and for 3 months following the last dose of POTELIGEO [see Use in Specific Populations (8.3)].

POTELIGEO® (mogamulizumab-kpkc)
Manufactured by:
Kyowa Kirin, Inc.
Princeton, NJ 08540
US License No. 2077

PATIENT INFORMATION
POTELIGEO® (poe–te–lig'–ee–oh)
(mogamulizumab-kpkc)
injection, for intravenous use

What is the most important information I should know about POTELIGEO?
POTELIGEO may cause serious side effects that can be severe, life-threatening or lead to death.
Call or see your healthcare provider right away if you develop any symptoms of the following problems or if these symptoms get worse:

- Skin problems. Signs and symptoms of skin reactions may include:

- skin pain
- itching
- skin blistering or peeling

- rash
- painful sores or ulcers in your mouth, nose, throat, or genital area

- Infusion reactions. Signs and symptoms of infusion reactions may include:

- chills or shaking
- redness on your face (flushing)
- itching or rash
- shortness of breath, coughing, or wheezing

- dizziness
- feeling like passing out
- tiredness
- fever

- Infections. Signs and symptoms of infection may include:

- fever, sweats, or chills
- nausea
- flu-like symptoms
- sore throat or difficulty swallowing

- shortness of breath
- diarrhea or stomach pain
- cough

- Autoimmune problems. Some people receiving POTELIGEO develop autoimmune problems (a condition where the immune cells in your body attack other cells or organs in the body). Some people who already have an autoimmune disease may get worse during treatment with POTELIGEO.
- Complications of stem cell transplantation that uses donor stem cells (allogeneic) after treatment with POTELIGEO. These complications can be severe and can lead to death. Your healthcare provider will monitor you for signs of complications if you have an allogeneic stem cell transplant.

Getting medical treatment right away may help keep these problems from becoming more serious.
Your healthcare provider will check you for these problems during treatment with POTELIGEO. Your healthcare provider may need to delay or completely stop treatment with POTELIGEO if you have severe side effects.

What is POTELIGEO?
POTELIGEO is a prescription medicine used to treat mycosis fungoides (MF) or Sézary syndrome (SS) in adults when you have tried at least one prior medicine (taken by mouth or injection) and it did not work or the disease has come back.
It is not known if POTELIGEO is safe and effective in children.

Before receiving POTELIGEO treatment, tell your healthcare provider about all your medical conditions, including if you:

- have had a severe skin reaction after receiving POTELIGEO.
- have had an infusion-related reaction during or after receiving POTELIGEO.
- have or have had liver problems including hepatitis B (HBV) infection.
- have a history of autoimmune problems
- have undergone or plan to have a stem cell transplant, using stem cells from a donor.
- have lung or breathing problems
- are pregnant or plan to become pregnant. It is not known if POTELIGEO will harm your unborn baby.
  - If you are able to become pregnant, your healthcare provider will do a pregnancy test before you start treatment with POTELIGEO.
  - Females who are able to become pregnant should use an effective method of birth control during treatment with POTELIGEO and for 3 months after the last dose of POTELIGEO. Talk to your healthcare provider about birth control methods that you can use during this time. Tell your healthcare provider right away if you become pregnant during treatment with POTELIGEO.
- are breastfeeding or plan to breastfeed. It is not known if POTELIGEO passes into your breast milk Talk to your healthcare provider about the best way to feed your baby during treatment with POTELIGEO.

Tell your healthcare provider about all the medicines you take, including prescription and over-the-counter medicines, vitamins, and herbal supplements.

How will I receive POTELIGEO?

- Your healthcare provider will give you POTELIGEO into your vein through an intravenous (IV) line over at least 60 minutes.
- POTELIGEO is usually given on days 1, 8, 15, and 22 of the first 28-day cycle, then on days 1 and 15 of each 28-day cycle thereafter.
- Your healthcare provider will decide how many treatments you need based on how well you respond and tolerate the treatment.
- If you miss any appointments call your healthcare provider as soon as possible.

What are the possible side effects of POTELIGEO?
POTELIGEO may cause serious side effects including:

- See "What is the most important information I should know about POTELIGEO?"

The most common side effects of POTELIGEO include:

- rash
- tiredness
- diarrhea

- muscle and bone pain
- upper respiratory tract infection

These are not all the possible side effects of POTELIGEO.
Call your doctor for medical advice about side effects. You may report side effects to FDA at 1-800-FDA-1088.

General information about the safe and effective use of POTELIGEO.
Medicines are sometimes prescribed for purposes other than those listed in a Patient Information leaflet. You can ask your healthcare provider or pharmacist for information about POTELIGEO that is written for healthcare professionals.

What are the ingredients in POTELIGEO?
Active ingredient: mogamulizumab-kpkc
Inactive ingredients: citric acid monohydrate, glycine, polysorbate 80, and Water for Injection, USP.
Manufactured by: Kyowa Kirin, Inc., Princeton, NJ 08540 U.S. License No. 2077
POTELIGEO is a registered trademark of Kyowa Kirin, Inc.
For more information, call 1-844-768-3544 or go to www.POTELIGEO.com.

This Patient Information has been approved by the U.S. Food and Drug Administration.

Issued: 3/2023

PRINCIPAL DISPLAY PANEL - 4 mg/mL Vial Carton

Rx only

NDC 42747-761-01

POTELIGEO®
(mogamulizumab-kpkc)

Injection

20 mg/5 mL (4 mg/mL)

For Intravenous Infusion

After Dilution

Single-dose vial.
Discard unused portion.